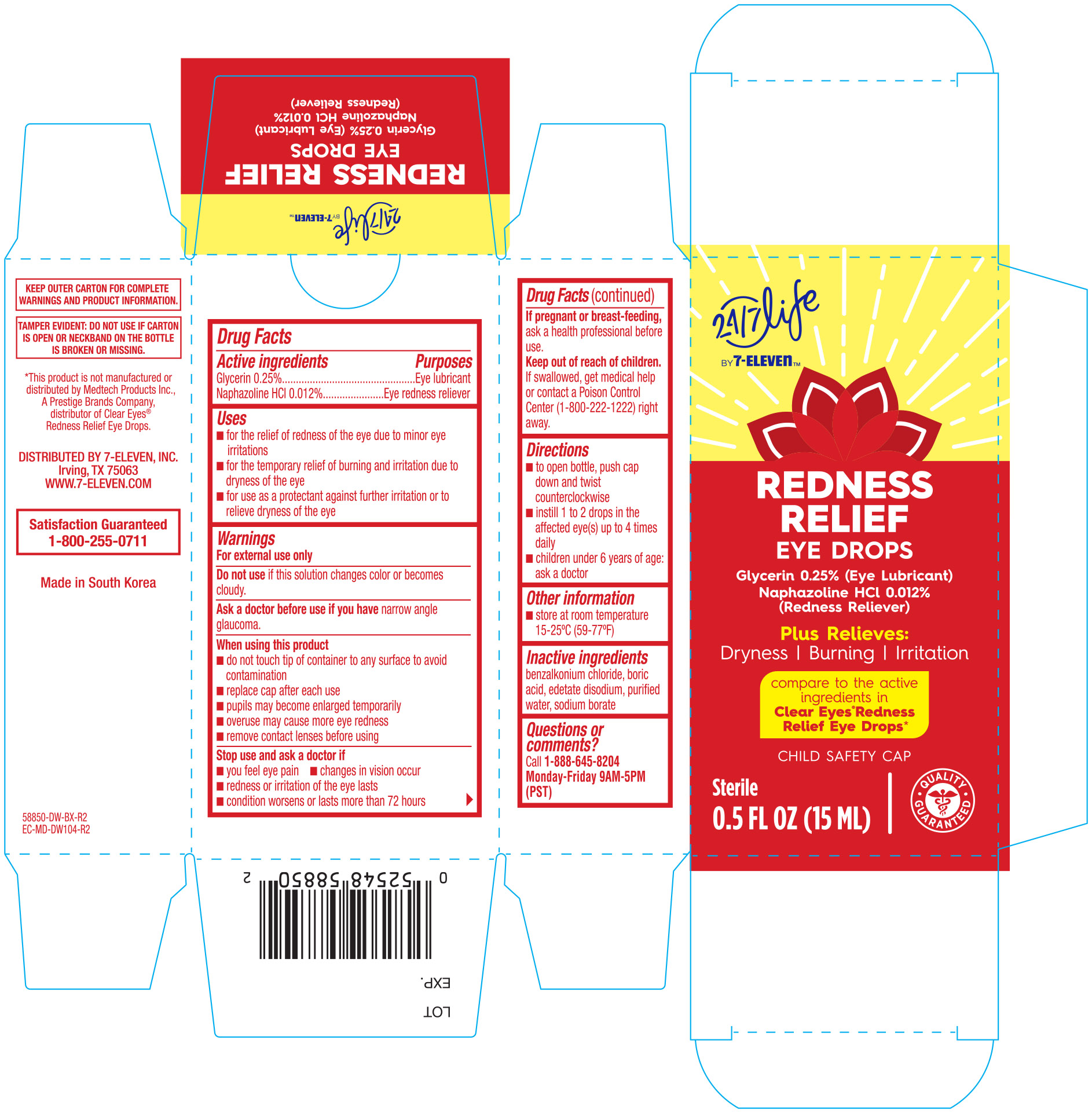 DRUG LABEL: 7 Select Redness Relief
NDC: 10202-850 | Form: SOLUTION/ DROPS
Manufacturer: 7-Select, Inc
Category: otc | Type: HUMAN OTC DRUG LABEL
Date: 20251031

ACTIVE INGREDIENTS: NAPHAZOLINE HYDROCHLORIDE 0.00012 mg/1 mL; GLYCERIN 0.0025 mg/1 mL
INACTIVE INGREDIENTS: BENZALKONIUM CHLORIDE; BORIC ACID; EDETATE DISODIUM; SODIUM BORATE; WATER

7 Select Redness Relief Lubricant 0.5oz (NBE Clear Eyes) 58850

Active ingredients Purpose

Glycerin 0.25%......................................Lubricant

Naphazoline HCI 0.012%.........................Redness reliever

Uses

- for the relief of redness of the eye due to minor eye irritations
- for the temporary relief of burning and irritation due to dryness of the eye
- for use as a protectant against further irritation or to relieve dryness of the eye

WARNINGS

Warings

For external use only

Do not use if solution changes color or becomes cloudy

Ask a doctor before use if you have narrow angle glaucoma

When using this product

- do not touch tip of container to any surface to avoid contamination
- replace cap after using
- pupils may become enlarged temporarily
- overuse may cause more eye redness
- remove contact lenses before using

Stop use and ask a doctor if

- you feel eye pain
- changes in vision occur
- redness or irritation of the eye lasts
- condition worsens or lasts more than 72 hours

PREGNANCY OR BREAST FEEDING

If pregnant or breast-feeding, ask a health professional before use.

Keep out of reach of children. If swallowed, get medical help or contact a Poison Control Center right away (1-800-222-1222).

Directions

- to open bottle, push cap down and twist counter-clockwise
- instill 1 to 2 drops in the affected eye(s) up to four time daily
- children under 6 years of age: ask a doctor

Other information

- store at room temperature 15-25 C (59-77F)

Inactive ingredients

benzalkonium chloride, boric acid, edetate disodium, purified water, sodium borate

DOSAGE AND ADMINISTRATION

Distributed by:

7-Elevin, Inc.

Irving TX 75063

www.7-eleven.com